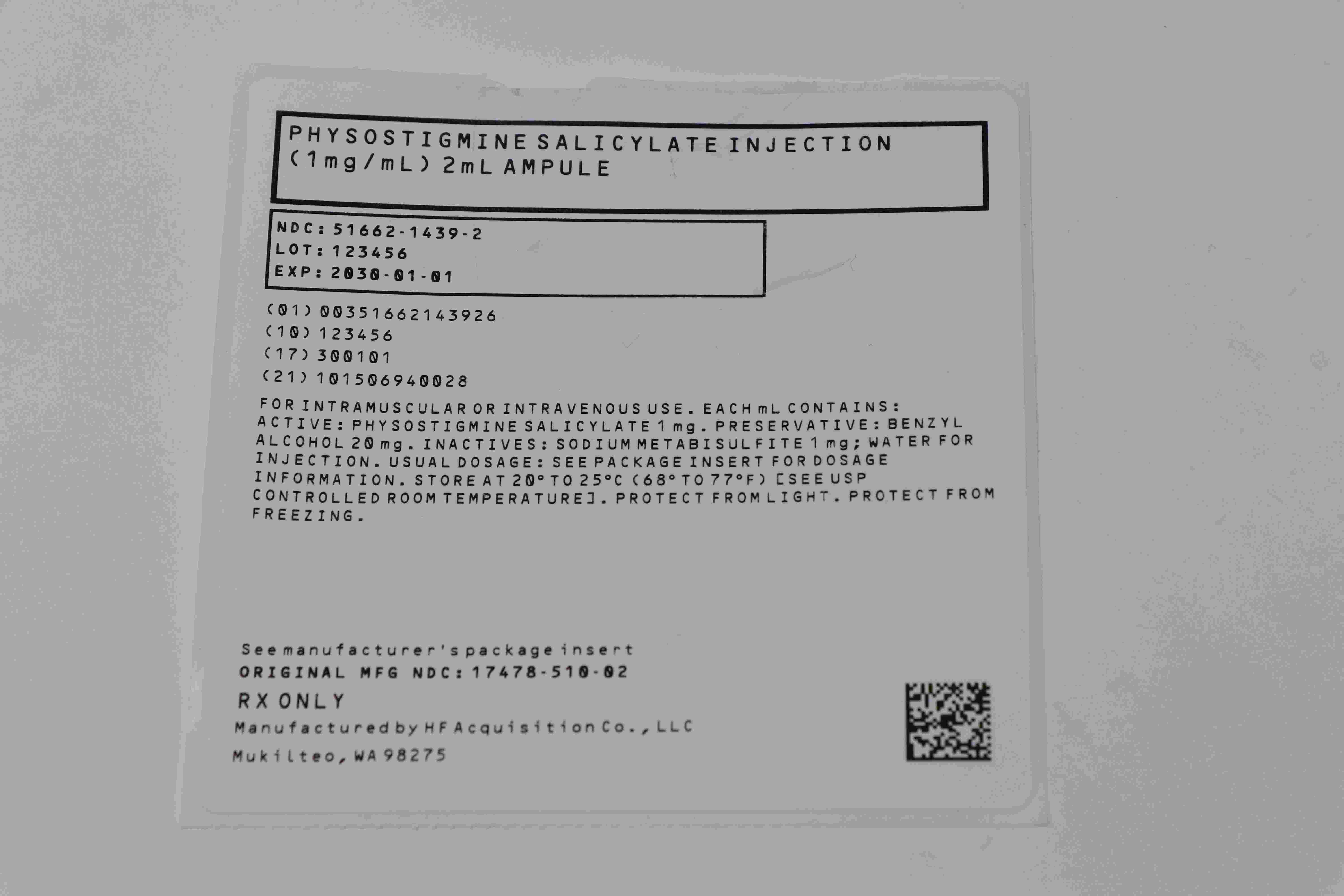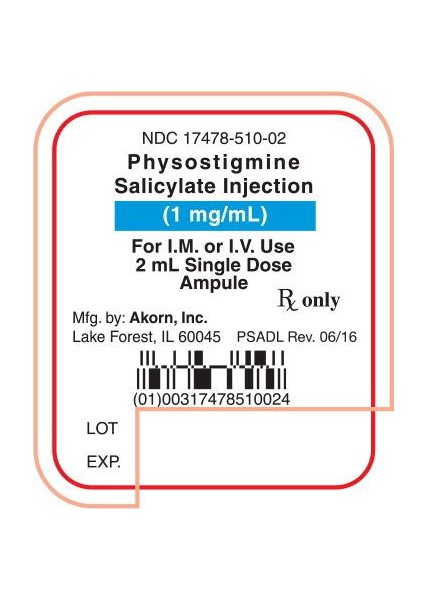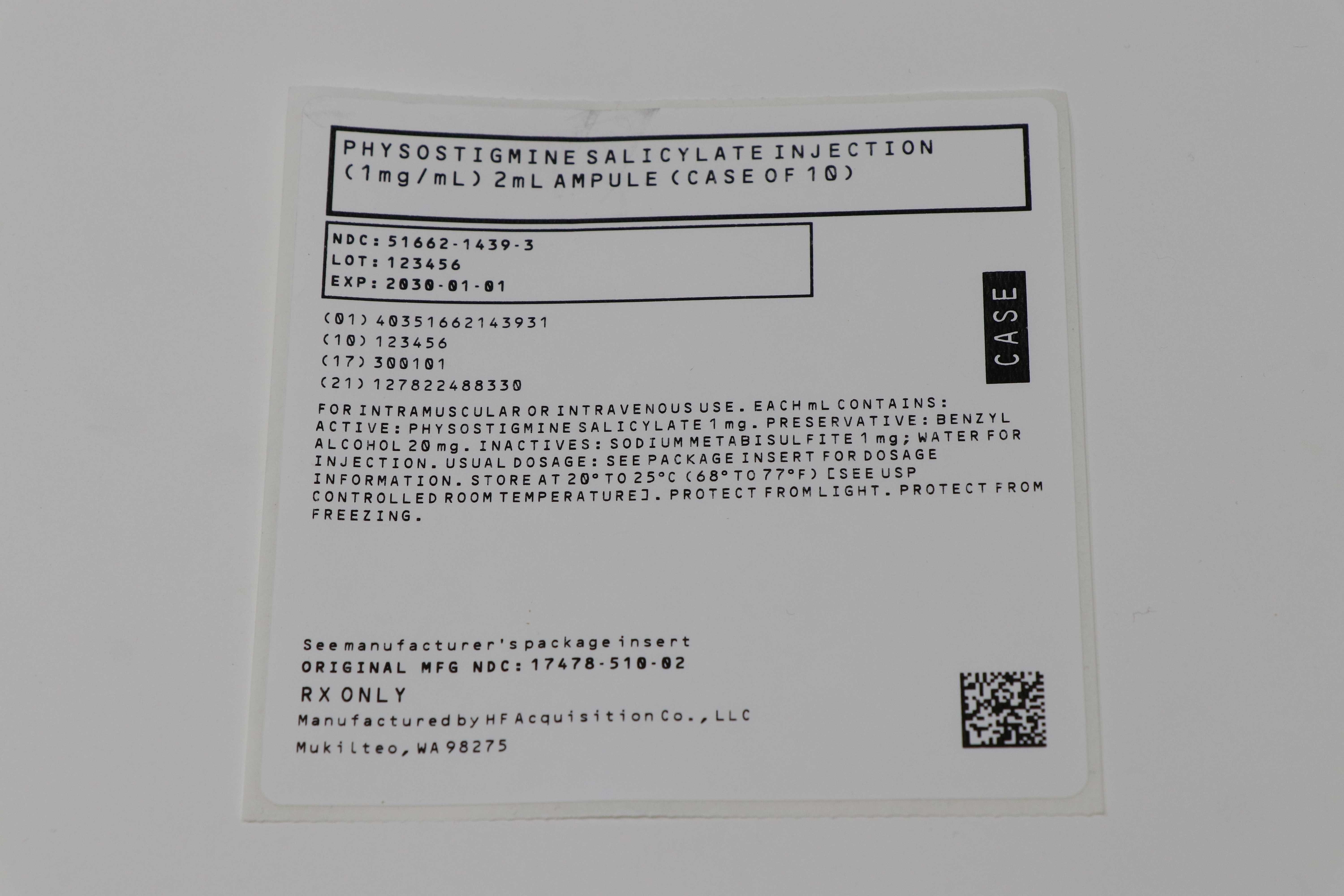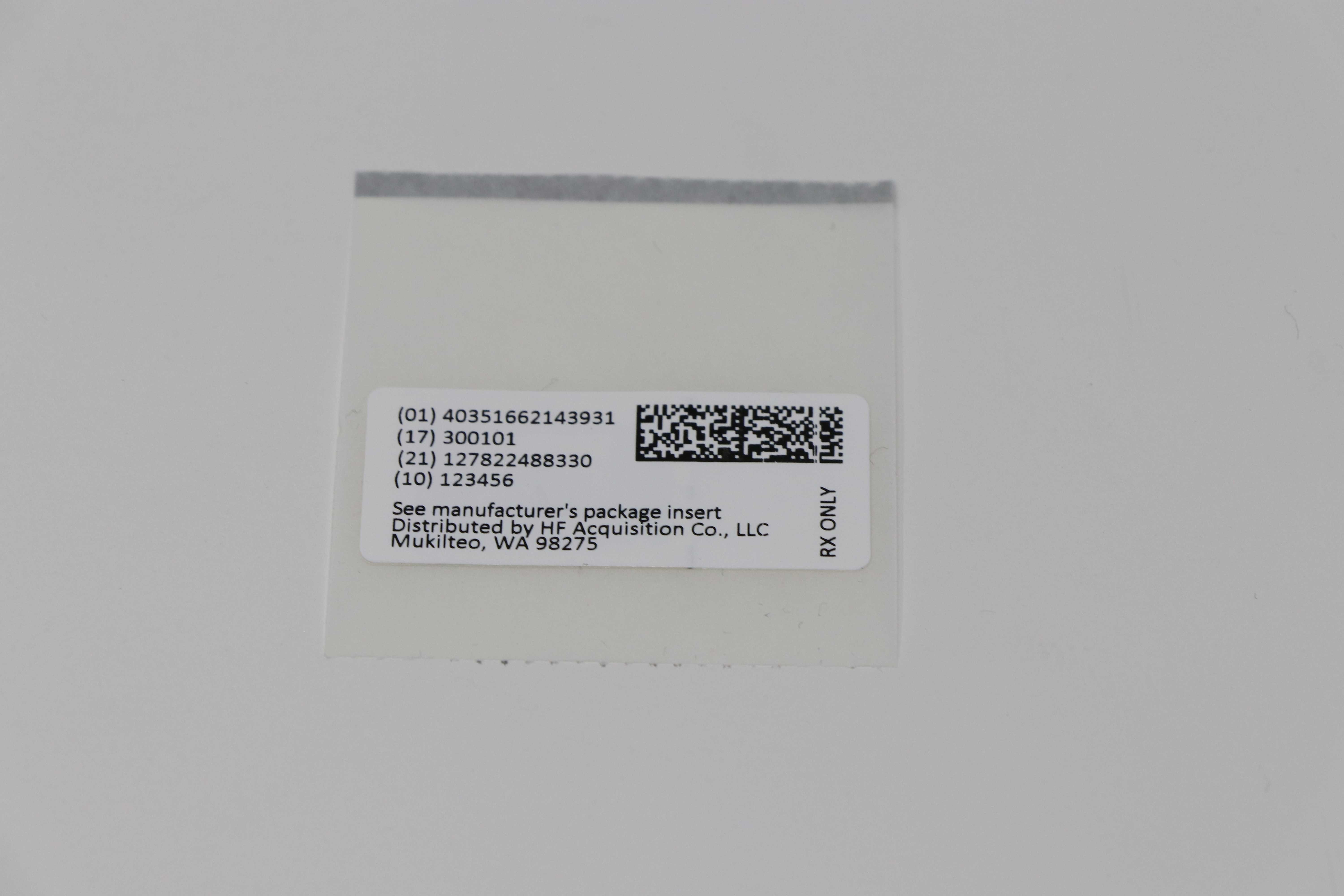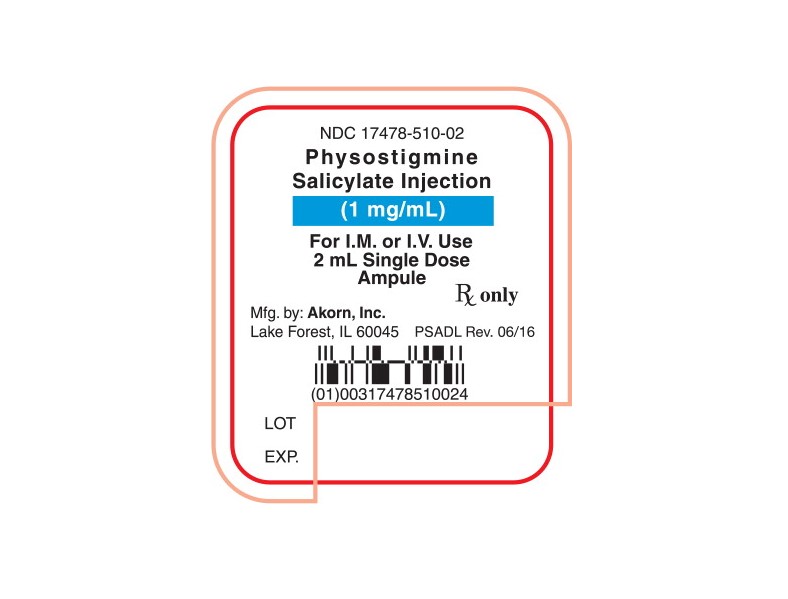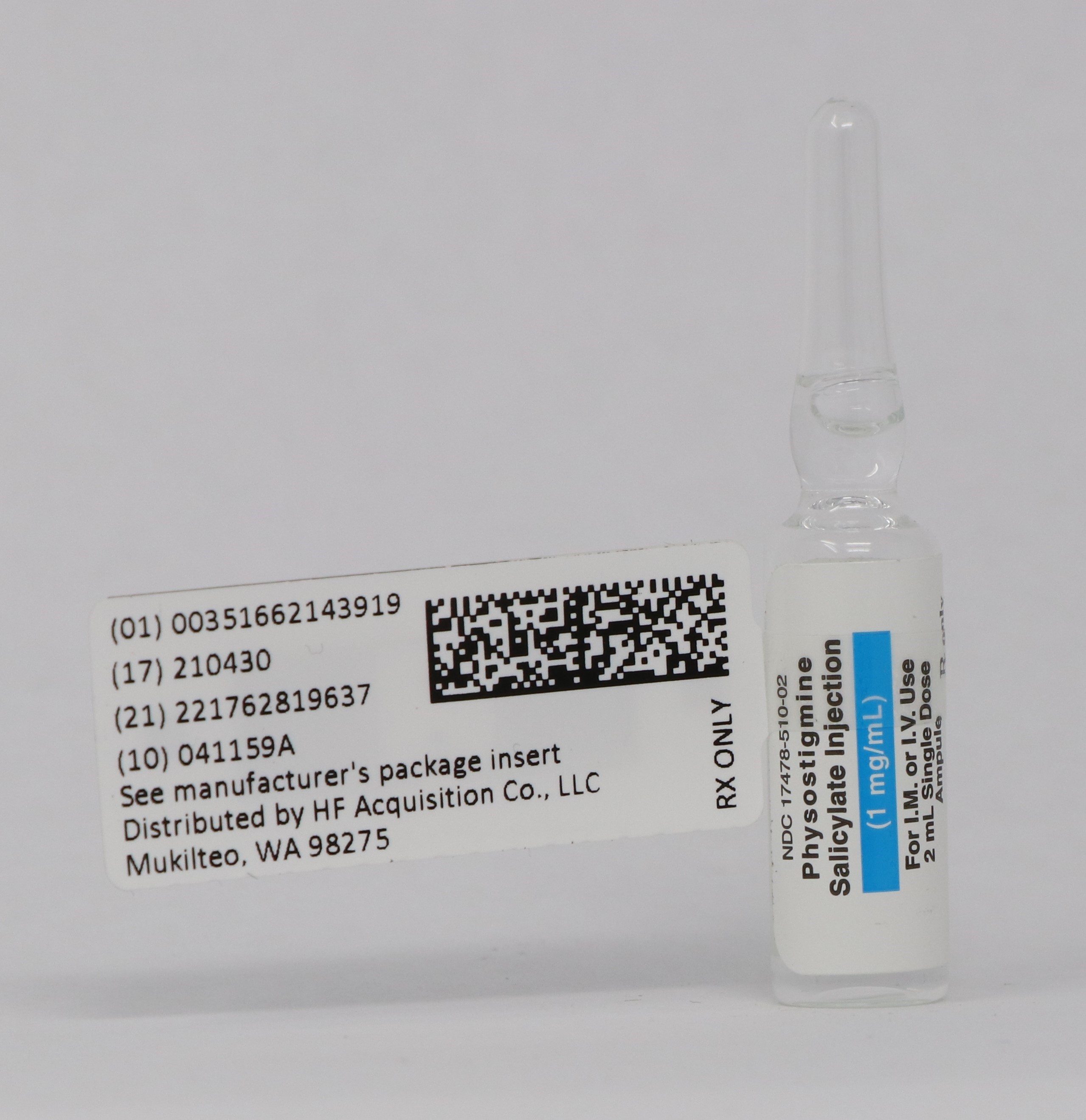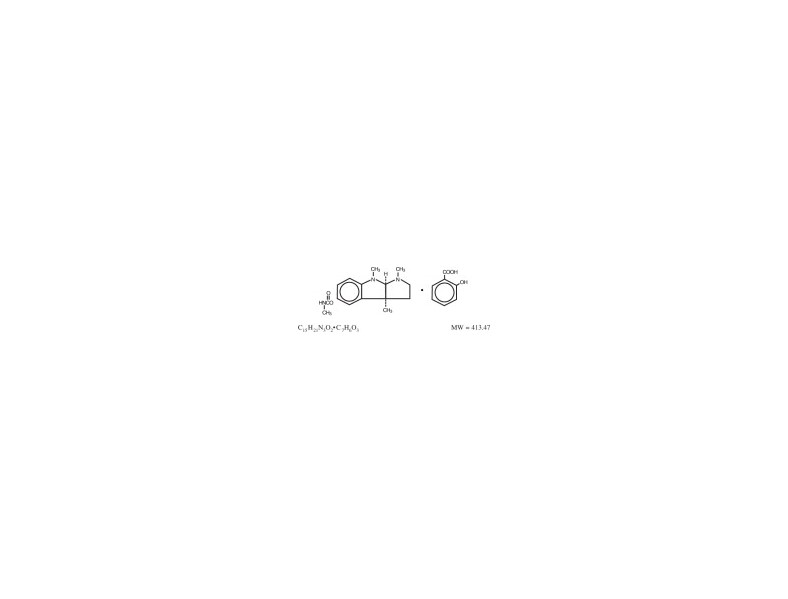 DRUG LABEL: PHYSOSTIGMINE SALICYLATE
NDC: 51662-1439 | Form: INJECTION
Manufacturer: HF Acquisition Co LLC, DBA HealthFirst
Category: prescription | Type: HUMAN PRESCRIPTION DRUG LABEL
Date: 20230109

ACTIVE INGREDIENTS: PHYSOSTIGMINE SALICYLATE 1 mg/1 mL
INACTIVE INGREDIENTS: SODIUM METABISULFITE; BENZYL ALCOHOL; WATER

PHYSOSTIGMINE SALICYLATE INJECTION (1mg/mL) 2mL AMPULE

SPL UNCLASSIFIED

Rx only

DESCRIPTION

Physostigmine Salicylate Injection is a derivative of the Calabar bean, and its active moiety, physostigmine, is also known as eserine. Its chemical structure is:

It is soluble in water and a 0.5% aqueous solution has a pH of 5.8.

Physostigmine Salicylate Injection is available in 2 mL ampules, each mL containing 1 mg of Physostigmine Salicylate in a vehicle composed of sodium metabisulfite 0.1%, benzyl alcohol 2.0% as a preservative in Water for Injection.

CLINICAL PHARMACOLOGY

Physostigmine Salicylate Injection is a reversible anticholinesterase which effectively increases the concentration of acetylcholine at the sites of cholinergic transmission. The action of acetylcholine is normally very transient because of its hydrolysis by the enzyme, acetylcholinesterase. Physostigmine Salicylate Injection inhibits the destructive action of acetylcholinesterase and thereby prolongs and exaggerates the effect of the acetylcholine.

Physostigmine Salicylate Injection contains a tertiary amine and easily penetrates the blood brain barrier, while an anticholinesterase, such as neostigmine, which has a quaternary ammonium ion is not capable of crossing the barrier. Physostigmine Salicylate Injection can reverse both central and peripheral anticholinergia. The anticholinergic syndrome has both central and peripheral signs and symptoms. Central toxic effects include anxiety, delirium, disorientation, hallucinations, hyperactivity and seizures. Severe poisoning may produce coma, medullary paralysis and death. Peripheral toxicity is characterized by tachycardia, hyperpyrexia, mydriasis, vasodilation, urinary retention, diminution of gastrointestinal motility, decrease of secretion in salivary and sweat glands, and loss of secretions in the pharynx, bronchi, and nasal passages.

Dramatic reversal of the effects of anticholinergic symptoms can be expected in minutes after the intravenous administration of Physostigmine Salicylate Injection, if the diagnosis is correct and the patient has not suffered anoxia or other insult. The duration of action of Physostigmine Salicylate Injection is relatively short, approximately 45 to 60 minutes.

Numerous drugs and some plants produce the anticholinergic syndrome either directly or as a side effect; this undesirable or potentially dangerous phenomenon may be brought about by either therapeutic doses or overdoses of the drugs. Such drugs include among others, atropine, other derivatives of the belladonna alkaloids, tricyclic antidepressants, phenothiazines, and antihistamines.

INDICATIONS & USAGE

To reverse the effect upon the central nervous system, caused by clinical or toxic dosages of drugs capable of producing the anticholinergic syndrome.

CONTRAINDICATIONS

Physostigmine Salicylate Injection should not be used in the presence of asthma, gangrene, diabetes, cardiovascular disease, mechanical obstruction of the intestine or urogenital tract or any vagotonic state, and in patients receiving choline esters and depolarizing neuromuscular blocking agents (decamethonium, succinylcholine).

For post-anesthesia, the concomitant use of atropine with physostigmine salicylate is not recommended, since the atropine antagonizes the action of physostigmine.

WARNINGS

Contains sodium bisulfite, a sulfite that may cause allergic-type reactions including anaphylactic symptoms and life-threatening or less severe asthmatic episodes in certain susceptible people. The overall prevalence of sulfite sensitivity in the general population is unknown and probably low. Sulfite sensitivity is seen more frequently in asthmatic than in non-asthmatic people.

If excessive symptoms of salivation, emesis, urination and defecation occur, the use of Physostigmine Salicylate Injection should be terminated. If excessive sweating or nausea occur, the dosage should be reduced.

Intravenous administration should be at a slow, controlled rate, no more than 1 mg per minute (see DOSAGE. Rapid administration can cause bradycardia, hypersalivation leading to a respiratory difficulties and possible convulsions.

An overdosage of Physostigmine Salicylate Injection can cause a cholinergic crisis.

PRECAUTIONS

Because of the possibility of hypersensitivity in an occasional patient, atropine sulfate injection should always be at hand since it is an antagonist and antidote for physostigmine.

USAGE IN PRENANCY

Safe use in pregnancy and lactation has not been established; therefore, use in pregnant women, nursing mothers or women who may become pregnant requires that possible benefits be weighed against possible hazards to mother and child.

ADVERSE REACTIONS

Nausea, vomiting and salivation; can be offset by reducing dosage. Bradycardia and convulsions, if intravenous administration is too rapid. See DOSAGE AND ADMINISTRATION.

OVERDOSAGE

Can cause a cholinergic crisis. Appropriate antidote is atropine sulfate.

DOSAGE & ADMINISTRATION

Past Anesthesia Care: 0.5 to 1.0 mg intramuscularly or intravenously. INTRAVENOUS ADMINISTRATION SHOULD BE AT A SLOW CONTROLLED RATE OF NO MORE THAN 1 MG PER MINUTE. Dosage may be repeated at intervals of 10 to 30 minutes if desired patient response is not obtained.

OVERDOSAGE OF DRUGS THAT CAUSE ANTICHOLINERGIC:

2.0 mg intramuscularly or INTRAVENOUSLY AT SLOW CONTROLLED RATE (SEE ABOVE). Dosage may be repeated if life threatening signs, such as arrhythmia, convulsions or coma occurs.

PEDIATRIC DOSAGE

Recommended dosage is 0.02 mg/kg; intramuscularly or by slow intravenous injection, no more than 0.5 mg per minute. If the toxic effects persist, and there is no sign of cholinergic effects, the dosage may be repeated at 5 to 10 minute intervals until a therapeutic effect is obtained or a maximum of 2 mg dosage is attained.

IN ALL CASES OF POISONING, THE USUAL SUPPORTIVE MEASURES SHOULD BE UNDERTAKEN.

HOW SUPPLIED

PHYSOSTIGMINE SALICYLATE INJECTION is supplied in the following dosage forms.
NDC 51662-1439-1
PHYSOSTIGMINE SALICYLATE INJECTION (1mg/mL) 2mL AMPULE

NDC 51662-1439-2
PHYSOSTIGMINE SALICYLATE INJECTION (1mg/mL) 2mL AMPULE, 1 AMPULE/POUCH

NDC 51662-1439-3
PHYSOSTIGMINE SALICYLATE INJECTION (1mg/mL) 2mL AMPULE, 1 AMPULE/POUCH, 10 POUCHES/CASE

HF Acquisition Co LLC, DBA HealthFirst
Mukilteo, WA 98275

STORAGE: Store at 20° to 25°C (68° to 77°F) [see USP Controlled Room Temperature].

SOME DRUGS WHICH PRODUCE THE ANTICHOLINERGIC SYNDROME

Amitriptyline, Amoxapine, Anisotropine, Atropine, Benztropine, Biperiden, Carbinoxamine, Clidinium, Cyclobenzaprine, Desipramine, Doxepin, Homatropine, Hyoscine, Hyoscyamine, Hyoscyamus, Imipramine, Lorazepam, Maprotiline, Mepenzolate, Nortriptyline, Propantheline, Protriptyline, Scopolamine, Trimipramine.

SOME PLANTS THAT PRODUCE THE ANTICHOLINERGIC SYNDROME

Black Henbane, Deadly Night Shade, Devil's Apple, Jimson Weed, Loco Seeds or Weeds, Matrimony Vine, Night Blooming Jessamine, Stinkweed.

PRINCIPAL DISPLAY PANEL, NDC 51662-1439-2 POUCH LABELING

NDC 51662-1439-2 POUCH LABELING

AMPULE LABELING

PRINCIPAL DISPLAY PANEL, NDC 51662-1439-3 CASE LABELING

51662-1539-3 CASE LABELING

SERIALIZED RFID LABELING